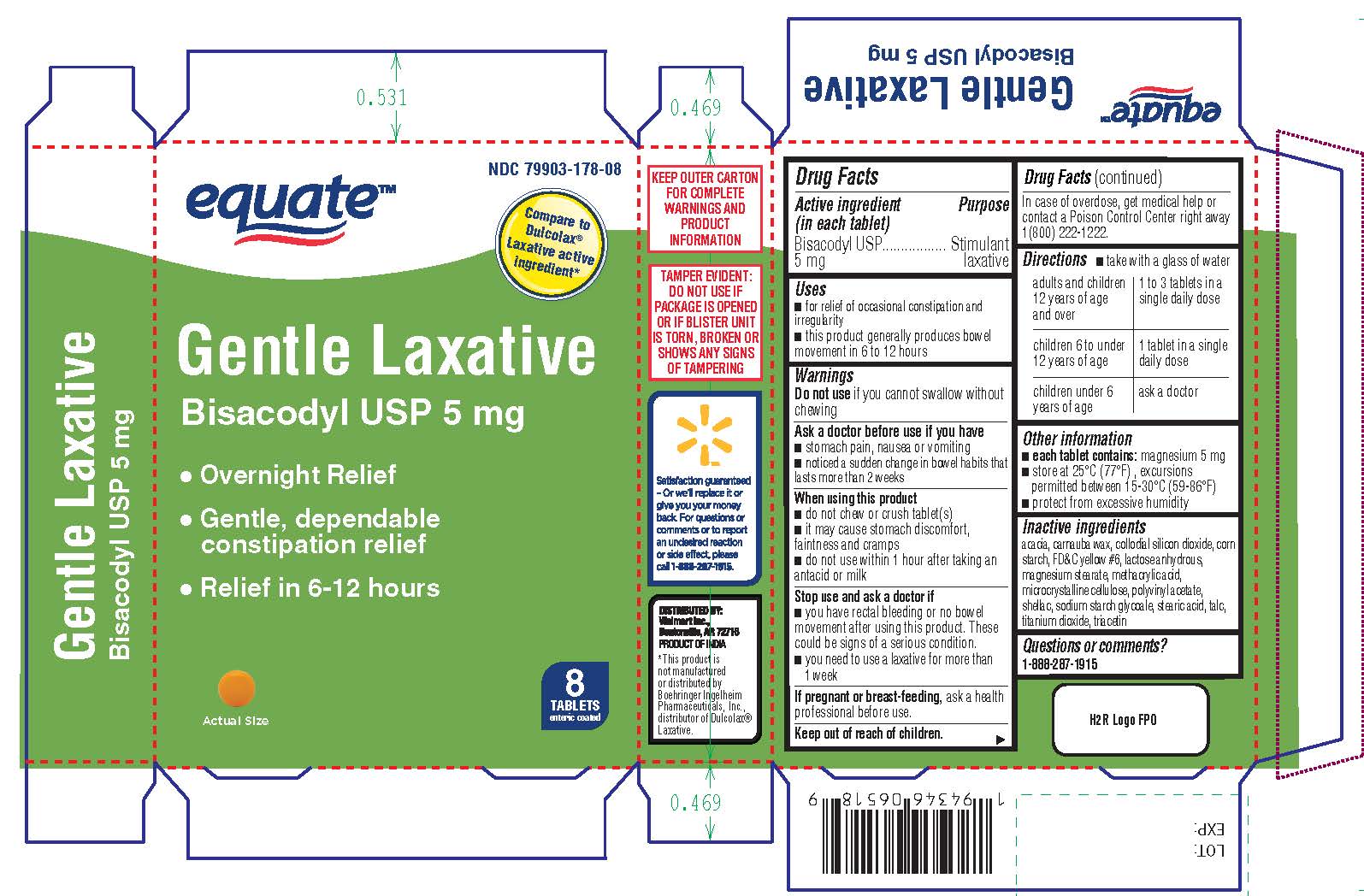 DRUG LABEL: GENTLE LAXATIVE
NDC: 79903-178 | Form: TABLET, DELAYED RELEASE
Manufacturer: Wal-Mart Stores Inc
Category: otc | Type: HUMAN OTC DRUG LABEL
Date: 20260126

ACTIVE INGREDIENTS: BISACODYL 5 mg/1 1
INACTIVE INGREDIENTS: ACACIA; ANHYDROUS LACTOSE; CARNAUBA WAX; SILICON DIOXIDE; STARCH, CORN; FD&C YELLOW NO. 6; METHACRYLIC ACID; MAGNESIUM STEARATE; CELLULOSE, MICROCRYSTALLINE; POLYVINYL ACETATE PHTHALATE; SHELLAC; SODIUM STARCH GLYCOLATE TYPE A; STEARIC ACID; TALC; TITANIUM DIOXIDE; TRIACETIN

GENTLE LAXATIVE

Active ingredient

(In each tablet)

Bisacodyl 5mg

Purpose

Stimulant Laxative

Uses

- for relief of occasional constipation and irregularity
- this product generally produces bowel movement in 6 to 12 hours

Warnings

Do not use if you cannot swallow without chewing

Ask a doctor before use if you have

- stomach pain, nausea or vomiting
- noticed a sudden change in bowel habits that lasts more than 2 weeks

When using this product

- do not chew or crush tablet(s)
- it may cause stomach discomfort, faintness and cramps
- do not use within 1 hour after taking an antacid or milk

Stop use and ask a doctor if

- you have rectal bleeding or no bowel movement after using this product. These could be signs of a serious condition.
- you need to use a laxative for more than 1 week

PREGNANCY OR BREAST FEEDING

If pregnant or breast-feeding, ask a health professional before use.

Keep out of reach of children.
In case of overdose, get medical help or contact a Poison Control Center right away 1(800) 222-1222.

Directions

- take with a glass of water
- adults and children 12 years and over: take 1 to 3 tablets in a single daily dose
- children 6 to under 12 years: take 1 tablet in a single daily dose
- children under 6 years: ask a doctor

Other information

- each tablet contains: magnesium 5 mg
- store at 25°C (77°F) , excursions permitted between 15-30°C (59-86°F)
- protect from excessive humidity

Inactive ingredients

acacia, carnauba wax, collodial silicon dioxide, corn starch, FD&C yellow #6, lactose anhydrous, magnesium stearate, methacrylic acid,
microcrystalline cellulose, polyvinyl acetate, shellac, sodium starch glycoale, stearic acid, talc, titanium dioxide, triacetin

Questions or comments?

1-888-287-1915

Distributed by:
Walmart Inc.
Bentonville, AR 72716
Product of India

*This product is not manufactured or distributed by Boehringer Ingelheim Pharmaceuticals, Inc., distributor of Dulcolax® Laxative.

DISPLAY PANEL

Compare to Dulcolax® Laxative active ingredient*

GENTLE LAXATIVE

BISACODYL 5 mg

- Overnight Relief
- Gentle, dependable constipation relief
- Relief in 6-12 hours

8 TABLETS

ENTERIC COATED